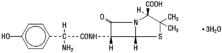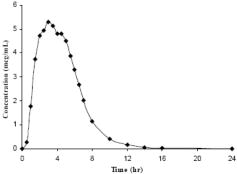 DRUG LABEL: Unknown
Manufacturer: MiddleBrook Pharmaceuticals, Inc.
Category: prescription | Type: HUMAN PRESCRIPTION DRUG LABEL WITH HIGHLIGHTS
Date: 20081208

HIGHLIGHTS OF PRESCRIBING INFORMATION

MOXATAG™ (amoxicillin extended-release) Tablets

To reduce the development of drug-resistant bacteria and maintain the effectiveness of MOXATAG and other antibacterial drugs, MOXATAG should be used only to treat or prevent infections that are proven or strongly suspected to be caused by bacteria.

1. INDICATIONS AND USAGE

MOXATAG is a penicillin-class antibacterial indicated for the treatment of tonsillitis and/or pharyngitis secondary to Streptococcus pyogenes in adults and pediatric patients 12 years or older. (1)

2. DOSAGE AND ADMINISTRATION

Tonsillitis and/or Pharyngitis: 775 mg once daily for 10 days with a meal.

Do not chew or crush tablet. (2)

3. DOSAGE FORMS AND STRENGTHS

Tablets: 775 mg (3)

4. CONTRAINDICATIONS

Patients with known serious hypersensitivity to amoxicillin or to other drugs in the same class or patients who have demonstrated anaphylactic reactions to beta-lactams (4)

5. WARNINGS AND PRECAUTIONS

- Serious and occasionally fatal hypersensitivity (anaphylactic) reactions have been reported in patients on penicillin therapy. Serious anaphylactic reactions require immediate emergency treatment with epinephrine. Oxygen, intravenous steroids, and airway management, including intubation, should also be administered as indicated. (5.1)
- Clostridium difficile associated diarrhea (ranging from mild diarrhea to fatal colitis): Evaluate if diarrhea occurs. (5.2)

6. ADVERSE REACTIONS

The most common drug-related adverse reactions (incidence≥1.0 %) are vulvovaginal mycotic infection, diarrhea, nausea, vomiting and headache. (6.1)

7. DRUG INTERACTIONS

- Probenecid decreases the renal tubular secretion of amoxicillin. Concurrent use of amoxicillin and probenecid may result in increased and prolonged blood levels of amoxicillin. (7.1)

8. USE IN SPECIFIC POPULATIONS

- Pediatrics: The safety and effectiveness of MOXATAG in pediatric patients younger than 12 years has not been established. (8.4)
- Renal Impairment: MOXATAG has not been studied in patients with renal impairment; however, a reduction of amoxicillin dose is generally recommended for patients with severe renal impairment. Therefore, MOXATAG is not recommended for use in patients with severe renal impairment (CrCl < 30 mL/min) or patients on hemodialysis. (8.6)

FULL PRESCRIBING INFORMATION

1. INDICATIONS AND USAGE

Tonsillitis and/or Pharyngitis

MOXATAG is a penicillin-class antibacterial indicated for the treatment of tonsillitis and/or pharyngitis secondary to Streptococcus pyogenes (S. pyogenes) in adults and pediatric patients 12 yrs and older.

To reduce the development of drug-resistant bacteria and maintain the effectiveness of MOXATAG and other antibacterial drugs, MOXATAG should be used only to treat or prevent infections that are proven or strongly suspected to be caused by susceptible bacteria. When culture and susceptibility information are available, they should be considered in selecting or modifying antibacterial therapy. In the absence of such data, local epidemiology and susceptibility patterns may contribute to the empiric selection of therapy.

2. DOSAGE AND ADMINISTRATION

Tonsillitis and/or Pharyngitis

The recommended dose of MOXATAG is 775 mg once daily taken within 1 hour of finishing a meal for 10 days. The full 10-day course of therapy should be completed for effective treatment of tonsillitis and/or pharyngitis secondary to S. pyogenes.

Do not chew or crush tablet.

3. DOSAGE FORMS AND STRENGTHS

775 mg blue film-coated, oval-shaped tablets printed with ”MB-111” on one side in black edible ink.

4. CONTRAINDICATIONS

MOXATAG is contraindicated in patients with known serious hypersensitivity to amoxicillin or to other drugs in the same class or patients who have demonstrated anaphylactic reactions to beta-lactams.

5. WARNINGS AND PRECAUTIONS

5.1 Anaphylaxis and Hypersensitivity Reactions

Serious and occasionally fatal hypersensitivity (anaphylactic) reactions have been reported in patients on penicillin therapy. Although anaphylaxis is more frequent following parenteral therapy, it has occurred in patients on oral penicillins. These reactions are more likely to occur in individuals with a history of penicillin hypersensitivity and/or a history of sensitivity to multiple allergens. There have been reports of individuals with a history of penicillin hypersensitivity who have experienced severe reactions when treated with cephalosporins. Before initiating therapy with MOXATAG, careful inquiry should be made concerning previous hypersensitivity reactions to penicillins, cephalosporins, or other allergens. If an allergic reaction occurs, MOXATAG should be discontinued and appropriate therapy instituted.

Serious anaphylactic reactions require immediate emergency treatment with epinephrine. Oxygen, intravenous steroids, and airway management, including intubation, should also be administered as indicated.

5.2 Clostridium difficile Associated Diarrhea (CDAD)

Clostridium difficile Associated Diarrhea (CDAD) has been reported with nearly all antibacterial agents, including amoxicillin, and may range in severity from mild diarrhea to fatal colitis. Treatment with antibacterial agents alters the normal flora of the colon leading to overgrowth of C. difficile. C. difficile produces toxins A and B which contribute to the development of CDAD. Hypertoxin producing strains of C. difficile cause increased morbidity and mortality, as these infections can be refractory to antimicrobial therapy and may require colectomy. CDAD must be considered in all patients who present with diarrhea following antibiotic use. Careful medical history is necessary since CDAD has been reported to occur over two months after the administration of antibacterial agents.

If CDAD is suspected or confirmed, ongoing antibiotic use not directed against C. difficile may need to be discontinued. Appropriate fluid and electrolyte management, protein supplementation, antibiotic treatment of C. difficile, and surgical evaluation should be instituted as clinically indicated.

5.3 Superinfections

The possibility of superinfections with mycotic or bacterial pathogens should be kept in mind during therapy. If superinfections occur, amoxicillin should be discontinued and appropriate therapy instituted.

5.4 Mononucleosis Rash

A high percentage of patients with mononucleosis who receive ampicillin develop an erythematous skin rash. Thus, ampicillin-class antibiotics should not be administered to patients with mononucleosis.

5.5 Development of Drug-Resistant Bacteria

Prescribing amoxicillin in the absence of proven or strongly suspected bacterial infection or treating prophylactically is unlikely to provide benefit to the patient and increases the risk of the development of drug-resistant bacteria.

5.6 False-Positive Urinary Glucose Tests

High urine concentrations of ampicillin may result in false-positive reactions when testing for the presence of glucose in urine using Clinitest®, Benedict's Solution or Fehling's Solution. Since this effect may also occur with amoxicillin, it is recommended that glucose tests based on enzymatic glucose oxidase reactions (such as Clinistix®) be used.

6. ADVERSE REACTIONS

Because clinical trials are conducted under widely varying conditions, adverse reaction rates observed in the clinical trials of a drug cannot be directly compared to rates in the clinical trials of another drug and may not reflect the rates observed in practice.

6.1 Clinical Study Experience

Tonsillitis and/or Pharyngitis

In a controlled Phase 3 trial, 302 adult and pediatric patients (≥ 12 years) were treated with MOXATAG 775 mg once-daily for 10 days and 306 adult and pediatric patients (≥ 12 years) were treated with penicillin VK 250 mg QID for 10 days.

In this clinical trial, the majority of treatment-emergent adverse reactions were of a mild and transient nature with similar frequency reported in both treatment groups. Discontinuation due to drug-related treatment-emergent adverse reactions occurred in 1.3 % of the MOXATAG-treated patients and 3.3 % of the penicillin VK-treated patients.

The most frequently reported adverse reactions (≥ 1%) which were suspected or probably drug-related are shown in Table 1.

Table 1. Drug-Related Treatment-Emergent Adverse Reactions by System Organ Class Experienced by ≥1% of Patients in Either Treatment Group – ITT/Safety Population
 | Number (%) of patients
System Organ Class/Preferred Term* | MOXATAG (N =302) | Pen VK (N = 306)
Patients with at least one drug-related treatment-emergent adverse event | 32 (10.6) | 45 (14.7)
Infections and infestations
Vulvovaginal mycotic infection | 6 (2.0) | 8 (2.6)
Gastrointestinal disorders
Diarrhea | 5 (1.7) | 6 (2.0)
Nausea | 4 (1.3) | 2 (0.7)
Vomiting | 2 (0.7) | 5 (1.6)
Abdominal pain | 1 (0.3) | 3 (1.0)
Nervous system disorders
Headache | 3 (1.0) | 3 (1.0)
*Presented in decreasing order of frequency in the MOXATAG column within each system organ class.

6.2 Adverse Reactions for Other Amoxicillin Products

The following adverse reactions have been reported for other products containing amoxicillin:

Infections and Infestations: Mucocutaneous candidiasis.

Gastrointestinal: Nausea, vomiting, diarrhea, and hemorrhagic/ pseudomembranous colitis.

Onset of pseudomembranous colitis symptoms may occur during or after antibiotic treatment.

Hypersensitivity Reactions: Anaphylaxis (See Warnings and Precautions)

Serum sickness like reactions, erythematous maculopapular rashes, erythema multiforme, Stevens-Johnson Syndrome, exfoliative dermatitis, toxic epidermal necrolysis, acute generalized exanthematous pustulosis, hypersensitivity vasculitis and urticaria have been reported. (NOTE: These hypersensitivity reactions may be controlled with antihistamines and, if necessary, systemic corticosteroids. Whenever such reactions occur, amoxicillin should be discontinued unless, in the opinion of the physician, the condition being treated is life-threatening and amenable only to amoxicillin therapy.)

Liver: A moderate rise in AST (SGOT) and/or ALT (SGPT) has been noted, but the significance of this finding is unknown. Hepatic dysfunction including cholestatic jaundice, hepatic cholestasis and acute cytolytic hepatitis have been reported.

Hemic and Lymphatic Systems: Anemia, including hemolytic anemia, thrombocytopenia, thrombocytopenic purpura, eosinophilia, leukopenia, and agranulocytosis have been reported during therapy with penicillins. These reactions are usually reversible on discontinuation of therapy and are believed to be hypersensitivity phenomena.

Central Nervous System: Reversible hyperactivity, agitation, anxiety, insomnia, confusion, convulsions, behavioral changes, and/or dizziness have been reported rarely.

Renal: Crystalluria has also been reported

Miscellaneous: Tooth discoloration (brown, yellow, or gray staining) has been rarely reported. Most reports occurred in pediatric patients. Discoloration was reduced or eliminated with brushing or dental cleaning in most cases.

7. DRUG INTERACTIONS

7.1 Probenecid

Probenecid decreases the renal tubular secretion of amoxicillin. Concurrent use of MOXATAG and probenecid may result in increased and prolonged blood levels of amoxicillin. The clinical relevance of this finding has not been evaluated.

7.2 Other Antibiotics

Chloramphenicol, macrolides, sulfonamides, and tetracyclines may interfere with the bactericidal effects of penicillin. This has been demonstrated in vitro; however, the clinical significance of this interaction is not well documented.

7.3 Oral Contraceptives

As with other antibiotics, amoxicillin may affect the gut flora, leading to lower estrogen reabsorption and potentially resulting in reduced efficacy of combined oral estrogen/progesterone contraceptives.

8. USE IN SPECIFIC POPULATIONS

8.1 Pregnancy

TERATOGENIC EFFECTS

Teratogenic Effects. Pregnancy Category B. Reproduction studies have been performed in mice and rats at doses up to 2000 mg/kg (12.5 and 25 times the human dose in mg/m^2) and have revealed no evidence of impaired fertility or harm to the fetus due to amoxicillin. There are, however, no adequate and well-controlled studies in pregnant women. Because animal reproduction studies are not always predictive of human response, this drug should be used during pregnancy only if clearly needed.

8.2 Labor and Delivery

Oral ampicillin-class antibiotics are poorly absorbed during labor. Studies in guinea pigs showed that intravenous administration of ampicillin slightly decreased the uterine tone and frequency of contractions but moderately increased the height and duration of contractions. However, it is not known whether use of amoxicillin in humans during labor or delivery has immediate or delayed adverse effects on the fetus, prolongs the duration of labor, or increases the likelihood that forceps delivery or other obstetrical intervention or resuscitation of the newborn will be necessary.

8.3 Nursing Mothers

Penicillins have been shown to be excreted in human milk. Amoxicillin use by nursing mothers may lead to sensitization of infants. Caution should be exercised when amoxicillin is administered to a nursing woman.

8.4 Pediatric Use

The safety and effectiveness of MOXATAG in pediatric patients 12 years of age and older have been established based on results of a clinical trial that included adults and pediatric patients (12 years or older). [see Clinical Studies (14)] Sixty three (21 %) of the study participants were pediatric patients 12 years of age or older. There were no significant differences in treatment response or adverse reactions from adults.

The safety and effectiveness of MOXATAG in pediatric patients younger than 12 years has not been established.

8.5 Geriatric Use

Clinical studies with MOXATAG did not include a sufficient number of patients aged 65 years and over to determine whether they respond differently from younger patients. Other reported clinical experiences with amoxicillin have not yet identified differences in responses between the elderly and younger patients, but a greater sensitivity of some older individuals cannot be ruled out.

This drug is known to be substantially excreted by the kidney, and the risk of adverse reactions to this drug may be greater in patients with impaired renal function. Because elderly patients are more likely to have decreased renal function, care should be taken in dose selection, and it may be useful to monitor renal function.

8.6 Renal Impairment

MOXATAG has not been studied in patients with renal impairment; however, a reduction of amoxicillin dose is generally recommended for patients with severe renal impairment. Therefore, MOXATAG is not recommended for use in patients with severe renal impairment (CrCl <30 mL/min) or patients on hemodialysis.

10. OVERDOSAGE

In case of overdose, discontinue medication, treat symptomatically, and institute supportive measures as required. If the overdose is very recent and there is no contraindication, an attempt at emesis or other means of removal of drug from the stomach may be performed. A prospective study of 51 pediatric patients at a poison-control center suggested that overdosages of less than 250 mg/kg of amoxicillin are not associated with significant clinical symptoms and do not require gastric emptying.

Interstitial nephritis resulting in oliguric renal failure has been reported in a small number of patients after overdosage with amoxicillin.

Crystalluria, in some cases leading to renal failure, has also been reported after amoxicillin overdosage in adult and pediatric patients. In case of overdosage, adequate fluid intake and diuresis should be maintained to reduce the risk of amoxicillin crystalluria.

Renal impairment appears to be reversible with cessation of drug administration. High blood levels may occur more readily in patients with impaired renal function because of decreased renal clearance of amoxicillin. Amoxicillin may be removed from circulation by hemodialysis.

For additional information about overdose treatment, call a poison control center (1-800-222-1222).

11. DESCRIPTION

MOXATAG (amoxicillin extended-release) tablets for oral administration are provided as blue film-coated tablets that contain 775 mg of amoxicillin as the trihydrate and are printed with ”MB-111” on one side in black edible ink.

Amoxicillin is a semi-synthetic antibiotic, an analog of ampicillin, with bactericidal activity against gram-positive and gram-negative microorganisms.

Chemically, amoxicillin is (2 S,5 R,6 R)-6-[(R)-(-)-2-amino-2-(p-hydroxyphenyl) acetamido]-3,3-dimethyl-7-oxo-4-thia-1-azabicyclo[3.2.0]heptane-2-carboxylic acid trihydrate. Its chemical name is amoxicillin. It may be represented structurally as:

The amoxicillin molecular formula is C16H19N3O5S·3H2O, and the molecular weight is 419.45.

MOXATAG is an extended release tablet formulation consisting of three components, one immediate-release and two delayed-release, each containing amoxicillin. The three components are combined in a specific ratio to prolong the release of amoxicillin from MOXATAG compared to immediate-release amoxicillin.

Each tablet contains amoxicillin, crospovidone, FD&C Blue #2 lake, hypromellose, hypromellose acetate succinate, iron oxide, magnesium stearate, methacrylic acid copolymer, microcrystalline cellulose, polyethylene glycol 400, polyoxyl 35 castor oil, shellac, colloidal silicon dioxide, sodium lauryl sulfate, talc, titanium dioxide, and triethyl citrate.

12. CLINICAL PHARMACOLOGY

12.1 Mechanism of Action

Amoxicillin is an antibacterial drug. [see Clinical Pharmacology (12.4)]

12.3 Pharmacokinetics

MOXATAG is an extended-release formulation of amoxicillin intended to provide once-daily dosing. Following the administration of MOXATAG with a low-fat meal in healthy subjects, mean amoxicillin AUC0-∞, Cmax, and Tmax values were 29.8 μg•h/mL, 6.6 μg/mL and 3.1 hours, respectively. The mean plasma concentration-time curve is shown below in Figure 1.

Figure 1. Mean Amoxicillin Plasma Concentrations Following a Single Oral Dose of MOXATAG With a Low-Fat Meal in Healthy Subjects (N=20)

Administration of MOXATAG with food decreases the rate, but not the extent of amoxicillin absorption. Compared to immediate-release amoxicillin suspension, the rate of amoxicillin absorption following administration of MOXATAG was slower, resulting in a lower Cmax and longer Tmax. Total amoxicillin exposure (AUC) achieved with MOXATAG is similar to that observed after oral administration of a comparable dose of immediate-release amoxicillin suspension.

Amoxicillin diffuses readily into most body tissues and fluids, with the exception of brain and spinal fluid, except when meninges are inflamed. Amoxicillin is approximately 20% protein bound in human serum.

Amoxicillin is primarily cleared by renal excretion. Approximately 60% of an oral dose of immediate-release amoxicillin is eliminated unchanged in urine. The half-life of amoxicillin after oral administration of MOXATAG is approximately 1.5 hours, similar to that of immediate-release amoxicillin. No accumulation of amoxicillin was observed after once-daily dosing of 775 mg of MOXATAG for 7 days.

Drug Interactions

In a study of healthy adult subjects, amoxicillin AUC was similar whereas Cmax increased approximately 35% following the administration of lansoprazole with MOXATAG given with food.

Probenecid decreases the renal tubular secretion of amoxicillin. Concurrent use of MOXATAG and probenecid may result in increased and prolonged blood levels of amoxicillin. The clinical relevance of this finding has not been evaluated.

12.4 Microbiology

Amoxicillin is a semi-synthetic antimicrobial belonging to the penicillin class of antimicrobials with activity against gram-positive bacteria.

Mechanism of Action

Amoxicillin exerts its bactericidal action against susceptible organisms during the stage of multiplication. It acts through the inhibition of biosynthesis of cell wall mucopeptide.

Mechanism of Resistance

To date there are no known mechanisms of resistance to penicillin or amoxicillin in Streptococcus pyogenes.

MOXATAG has been shown to be active in vitro against isolates of the microorganism S. pyogenes and in clinical infections as described in the INDICATIONS AND USAGE section.

Facultative Gram-Positive Bacteria:

Streptococcus pyogenes

The following in vitro data are available, but their clinical significance is unknown. At least 90% of the following microorganisms exhibit an in vitro minimum inhibitory concentration (MIC) less than or equal to the susceptibility breakpoint of amoxicillin (as determined by susceptibility tests using the class representative agents penicillin or ampicillin).

Facultative Gram-Positive Bacteria:

Streptococcus spp. (Group B, C, and G; β-hemolytic)

Susceptibility Test Methods:

When available, the clinical microbiology laboratory should provide cumulative results of the in vitro susceptibility test results for antimicrobial drugs used in local hospitals and practice areas to the physician as periodic reports that describe the susceptibility profile of nosocomial and community-acquired pathogens. These reports should aid the physician in selecting the most effective antimicrobial.

Susceptibility testing of penicillins (such as amoxicillin) and other β-lactams approved by FDA for the treatment of Group A streptococcus (S. pyogenes) is not routinely necessary for clinical purposes. Isolates of Group A streptococcus resistant to amoxicillin have not been recognized and therefore all isolates can be considered susceptible to amoxicillin However, susceptibility tests can be conducted using dilution or diffusion techniques employing penicillin or ampicillin to predict susceptibility to amoxicillin.

Dilution Techniques

Quantitative methods are used to determine antimicrobial MICs. These MICs provide estimates of the susceptibility of bacteria to antimicrobial compounds. The MICs should be determined using a standardized procedure^1,3. Standardized procedures are based on a dilution method (broth or agar) or equivalent with standardized inoculum concentrations and standardized concentrations of penicillin or ampicillin. The susceptibility of Group A streptococcus to penicillin or amoxicillin should be interpreted according to the criteria in Table 2.

Diffusion Technique

Quantitative methods that require measurement of zone diameters also provide reproducible estimates of the susceptibility of bacteria to antimicrobial compounds. One such standardized procedure^2 requires the use of a standardized inoculum concentration. This procedure uses paper disks impregnated with 10 units penicillin or 10 mcg ampicillin to test the susceptibility of S. pyogenes to penicillin or amoxicillin. Reports from the laboratory providing results of the standard single-disk susceptibility test should be interpreted according to the criteria in Table 2

Table 2. Susceptibility Test Results Interpretive Criteria for Beta-Hemolytic Streptococci including Streptococcus pyogenes
Antimicrobial | Minimum Inhibitory Concentration (mcg/mL) | Disk Diffusion (zone diameter in mm)
Penicillin | ≤0.12 = Susceptible | ≥24 = Susceptible
Ampicillin | ≤0.25 = Susceptible | ≥24 = Susceptible

The current absence of data on resistant isolates precludes defining any categories other than “Susceptible”. Isolates yielding results suggestive of a “nonsusceptible” category should be retested, and if the result is confirmed, the isolate should be submitted to a reference laboratory for further testing.

Quality Control

Standardized susceptibility test procedures require the use of laboratory controls to monitor and ensure the accuracy and precision of the supplies and reagents used in the assay, and the techniques of the individuals performing the test. Standard penicillin or ampicillin powders should provide the MIC ranges provided in Table 3. For the disk diffusion technique using the 10 unit penicillin disk or 10 μg ampicillin disk the criteria in Table 3 should be achieved.

Table 3. Acceptable Quality Control Ranges for Susceptibility Testing
QC Organism | Antimicrobial | Minimum Inhibitory Concentration (mcg/mL) | Disk Diffusion (zone diameter in mm)
Streptococcus pneumoniae | Penicillin | 0.25 – 1 | 24 – 30
ATCC 49619 | Ampicillin | 0.06 – 0.25 | 30 - 36
ATCC = American Type Culture Collection

13. NONCLINICAL TOXICOLOGY

13.1 Carcinogenesis, Mutagenesis, Impairment of Fertility

Long-term studies in animals have not been performed to evaluate carcinogenic potential. Studies to detect mutagenic potential of amoxicillin alone have not been conducted; however, the following information is available from tests on a 4:1 mixture of amoxicillin and potassium clavulanate (Augmentin). Augmentin was non-mutagenic in the Ames bacterial mutation assay, and the yeast gene conversion assay. Augmentin was weakly positive in the mouse lymphoma assay, but the trend toward increased mutation frequencies in this assay occurred at doses that were also associated with decreased cell survival. Augmentin was negative in the mouse micronucleus test, and in the dominant lethal assay in mice. Potassium clavulanate alone was tested in the Ames bacterial mutation assay and in the mouse micronucleus test, and was negative in each of these assays. In a multi-generation reproduction study in rats, no impairment of fertility or other adverse reproductive effects were seen at doses up to 500 mg/kg (approximately 6 times the human dose in mg/m^2).

14. CLINICAL STUDIES

In a randomized, parallel-group, multi-center, double-blind, double-dummy study in adults and pediatrics (age≥ 12 years) with tonsillitis and/or pharyngitis secondary to S. pyogenes, MOXATAG 775 mg QD for 10 days was non-inferior to penicillin VK 250 mg QID for 10 days.

Using strict evaluability and microbiologic response criteria 4-8 days post-therapy, the following bacteriological eradication rates and statistical outcomes in the per-protocol (PPb) and modified intent-to-treat (mITT) populations were obtained (Table 4). The mITT population included all randomized patients with a positive throat culture for S. pyogenes at baseline. The PPb population included mITT patients who had post-therapy cultures, were compliant with treatment, and didn't have major protocol violations.

Table 4. Bacteriological Eradication Rates in Patients with Tonsillitis and/or Pharyngitis
Study Population | MOXATAG | Penicillin VK | Rate Difference 95% CI (%)
PPb | 198/233 (85.0%) | 191/229 (83.4%) | 1.6 (-5.1, 8.2)
mITT | 204/256 (79.7%) | 206/264 (78.0%) | 1.7 (-5.4, 8.7)

15. REFERENCES

1. Clinical and Laboratory Standards Institute (CLSI). Methods for Dilution Antimicrobial Susceptibility Tests for Bacteria That Grow Aerobically; Approved Standard—7th ed Clinical and Laboratory Standards Institute document M7-A7. Clinical and Laboratory Standards Institute, 940 West Valley Road, Suite 1400, Wayne, Pennsylvania 19087-1898 USA, 2006.
2. CLSI. Performance Standards for Antimicrobial Disk Susceptibility Tests; Approved Standard—9th ed. CLSI document M2-A9 CLSI, Wayne, PA 19087-1898 2006.
3. CLSI. Performance Standards for Antimicrobial Susceptibility Testing; 17th Informational Supplement. CLSI document M100-S17 CLSI, Wayne, PA 19087-1898, 2007.

16. HOW SUPPLIED/STORAGE AND HANDLING

MOXATAG tablets for oral administration are provided as blue film-coated, oval-shaped tablets that contain 775 mg of amoxicillin as the trihydrate. The tablets are printed with “MB-111” on one side in black edible ink. MOXATAG is packaged in bottles and blister cards as follows:

- Bottles of 30 NDC 11042-142-03
- 10 Tablet Card
  (1 tablet per blister cavity) NDC 11042-142-02

Storage

Store at 25º C (77º F); excursions permitted to 15–30º C (59–86º F) [See USP Controlled Room Temperature.]

17. PATIENT COUNSELING INFORMATION

17.1 Instructions for Administration of MOXATAG

Patients should be informed that the recommended dose of MOXATAG is 775 mg once daily taken with food for 10 days. MOXATAG should be taken within 1 hour of finishing a meal and at approximately the same time every day.The full 10 day course of therapy should be completed for effective treatment of tonsillitis and/or pharyngitis secondary to S. pyogenes. Patients should be instructed not to chew or crush the tablet. No other forms of immediate-release amoxicillin can be substituted for MOXATAG.

17.2 Hypersensitivity Reactions

Patients should be informed that serious and occasionally fatal hypersensitivity (anaphylactic) reactions have been reported while on penicillin therapy. Patients should be questioned regarding any hypersensitivity reactions to penicillins, cephalosporins or other allergens. Whenever such reactions occur, the patient should be instructed to contact their physician immediately. Serious anaphylactic reactions require immediate emergency treatment with epinephrine. Oxygen, intravenous steroids, and airway management, including intubation, should also be administered as indicated.

17.3 Clostridium difficile Associated Diarrhea

Patients should be informed that diarrhea is a common problem caused by antibiotics which usually ends when the antibiotic is discontinued. Sometimes after starting treatment with antibiotics, patients can develop watery and bloody stools (with or without stomach cramps and fever) even as late as two or more months after having taken the last dose of the antibiotic. If this occurs, patients should contact their physician as soon as possible.

AUGMENTIN is a registered trademark of GlaxoSmithKline.

CLINITEST is a registered trademark of Miles, Inc.

CLINISTIX is a registered trademark of Bayer Corporation.

MOXATAG is a trademark of MiddleBrook Pharmaceuticals, Inc., all rights reserved.

Manufactured in Clonmel, Ireland by Stada Production Ireland for
MiddleBrook Pharmaceuticals, Inc., Germantown, Maryland 20876

U.S. Patents 6,544,555; 6,669,948; 6,723,341

Issue Date 06/08
PC2049L/1
Copyright © 2008, MiddleBrook Pharmaceuticals, Inc. All rights reserved.